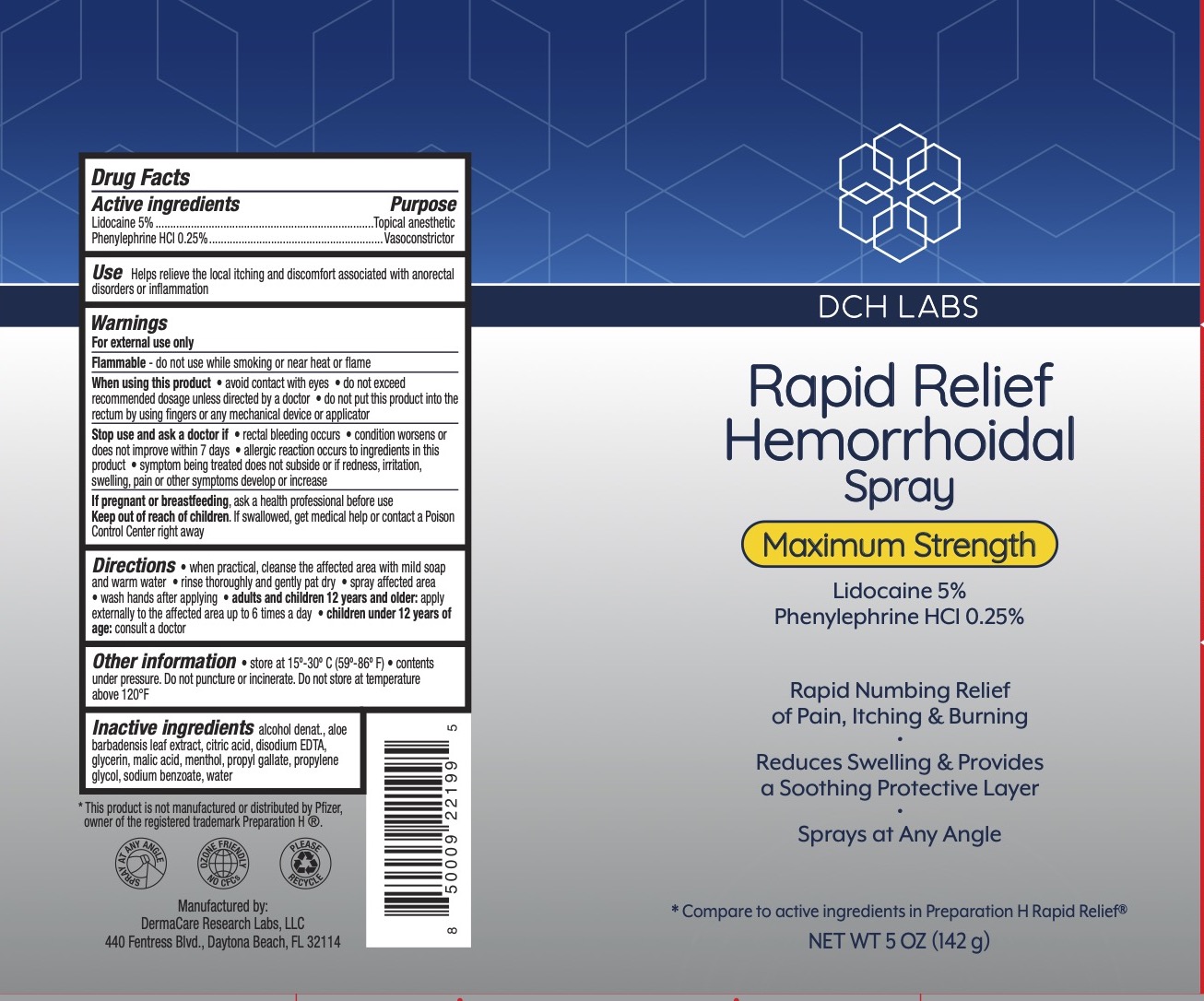 DRUG LABEL: DCH Rapid Relief Hemorrhoidal
NDC: 72839-263 | Form: SPRAY
Manufacturer: Derma Care Research Labs
Category: otc | Type: HUMAN OTC DRUG LABEL
Date: 20241219

ACTIVE INGREDIENTS: LIDOCAINE 5 g/100 g; PHENYLEPHRINE HYDROCHLORIDE 0.25 g/100 g
INACTIVE INGREDIENTS: ALOE; MENTHOL; ALCOHOL; PROPYLENE GLYCOL; PROPYL GALLATE; SODIUM BENZOATE; EDETATE DISODIUM; CITRIC ACID MONOHYDRATE; WATER; GLYCERIN; MALIC ACID

DCH Rapid Relief Hemorrhoidal Spray

ACTIVE INGREDIENT

Lidocaine 5%, Phenylephrine HCl 0.25%,

PURPOSE

Topical Anesthetic, Vasoconstrictor

INDICATIONS AND USAGE

Helps relieve the local itching and discomfort associated with anorectal disorders or inflammation.

WARNINGS

For external use only.

Flammable--do not use while smoking or near heat or flame.

When using this product avoid contact with eyes, contents under pressure. Do not puncture or incinerate. Do not store at temperatures above 120F, do not exceed recommended daily dosage unless directed by a doctor, do not put this product in the rectum by using fingers or any mechanical device or applicator.

Ask a doctor before use if you have heart disease, high blood pressure, thyroid disease, diabetes, difficulty in urination due to enlargement of the prostate gland, presently taking a prescription for high blood pressure or depression.

Stop use and ask a doctor if rectal bleeding occurs, the condition worsens or symptoms does not improve within 7 days, allergic reaction occurs to ingredients in this product, symptom being treated does not subside or if redness, irritation, swelling, pain or other symptoms develop or increase.

PREGNANCY OR BREAST FEEDING

Ask a healthcare or professional before use.

KEEP OUT OF REACH OF CHILDREN

If swallowed, seek medical help or contact a Poison Control Center right away.

DOSAGE AND ADMINISTRATION

When practical, cleanse the affected area with mild soap and warm water, rinse thoroughly, and gently pat dry. Spray the affected area, wash hands after applying. Adults and children 12 years and older: apply externally to the affected area up to 6 times a day. Children under 12 years of age: consult a doctor.

INACTIVE INGREDIENT

Alcohol, Aloe Barbadensis Leaf Extract, Citric Acid, Disodium EDTA, Glycerin, Malic Acid, Menthol, Propyl Gallate, Propylene Glycol, Sodium Benzoate, Water.